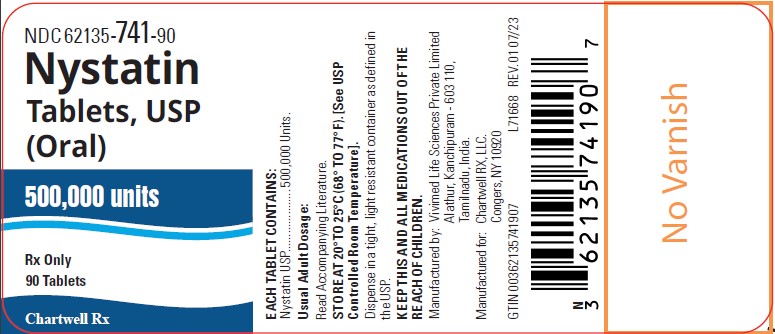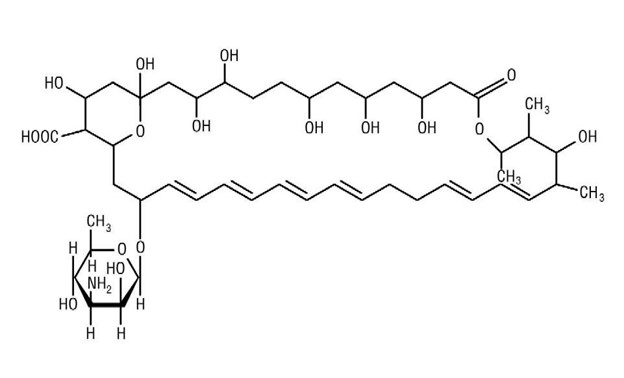 DRUG LABEL: Nystatin
NDC: 62135-741 | Form: TABLET, FILM COATED
Manufacturer: Chartwell RX, LLC
Category: prescription | Type: HUMAN PRESCRIPTION DRUG LABEL
Date: 20251217

ACTIVE INGREDIENTS: NYSTATIN 500000 [USP'U]/1 1
INACTIVE INGREDIENTS: STARCH, CORN; SUCROSE; HYDROXYPROPYL CELLULOSE (90000 WAMW); ANHYDROUS DIBASIC CALCIUM PHOSPHATE; MICROCRYSTALLINE CELLULOSE; TALC; MAGNESIUM STEARATE; HYPROMELLOSE 2910 (6 MPA.S); HYPROMELLOSE 2910 (3 MPA.S); POLYETHYLENE GLYCOL 400; POLYETHYLENE GLYCOL 8000; TITANIUM DIOXIDE; FD&C YELLOW NO. 6; FD&C RED NO. 40; FD&C BLUE NO. 2; POLYSORBATE 80

Nystatin Tablets, USP (Oral)
Rx only

DESCRIPTION

Nystatin, USP is an antimycotic polyene antibiotic obtained from Streptomyces noursei. Its structural formula:

C47H75NO17 M.W. 926.13

Nystatin tablets, USP are for oral administration and contain 500,000 units of nystatin, USP per tablet.
Nystatin tablets, USP contain the inactive ingredients: corn starch, confectioner sugar, dibasic calcium phosphate, FD&C yellow #6, FD&C red #40, FD&C blue #2, hydroxypropyl cellulose, hypromellose, microcrystalline cellulose, magnesium stearate, polyethylene glycol, polysorbate 80, talc and titanium dioxide.

CLINICAL PHARMACOLOGY

Pharmacokinetics

Gastrointestinal absorption of nystatin is insignificant. Most orally administered nystatin is passed unchanged in the stool. In patients with renal insufficiency receiving oral therapy with conventional dosage forms, significant plasma concentrations of nystatin may occasionally occur.

Microbiology

Nystatin is both fungistatic and fungicidal in vitroagainst a wide variety of yeasts and yeast-like fungi. Candida albicansdemonstrates no significant resistance to nystatin in vitroon repeated subculture in increasing levels of nystatin; other Candidaspecies become quite resistant. Generally, resistance does not develop in vivo. Nystatin acts by binding to sterols in the cell membrane of susceptible Candidaspecies with a resultant change in membrane permeability allowing leakage of intracellular components. Nystatin exhibits no appreciable activity against bacteria, protozoa, or viruses.

INDICATIONS AND USAGE

Nystatin Tablets are intended for the treatment of non-esophageal mucus membrane gastrointestinal candidiasis.

CONTRAINDICATIONS

Nystatin tablets are contraindicated in patients with a history of hypersensitivity to any of their components.

PRECAUTIONS

General

This medication is not to be used for the treatment of systemic mycoses. Discontinue treatment if sensitization or irritation is reported during use.

Carcinogenesis, Mutagenesis, Impairment of Fertility

No long-term animal studies have been performed to evaluate carcinogenic potential. There also have been no studies to determine mutagenicity or whether this medication affects fertility in males or females.

Pregnancy

Teratogenic Effects

Category C

Animal reproduction studies have not been conducted with nystatin. It is also not known whether nystatin can cause fetal harm when administered to a pregnant woman or can affect reproduction capacity. Nystatin should be given to a pregnant woman only if clearly needed.

Nursing Mothers

It is not known whether nystatin is excreted in human milk. Because many drugs are excreted in human milk, caution should be exercised when nystatin is administered to a nursing woman.

ADVERSE REACTIONS

Nystatin is well tolerated even with prolonged therapy. Oral irritation and sensitization have been reported. (See PRECAUTIONS: General.)

Gastrointestinal

Diarrhea (including one case of bloody diarrhea), nausea, vomiting, gastrointestinal upset/disturbances.

Dermatologic

Rash, including urticaria has been reported rarely. Stevens-Johnson syndrome has been reported very rarely.

Other

Tachycardia, bronchospasm, facial swelling, and nonspecific myalgia have also been rarely reported.

To report SUSPECTED ADVERSE REACTIONS, contact Chartwell RX, LLC. at 1-845-232-1683 or FDA at 1-800-FDA-1088 or www.fda.gov/medwatch.

OVERDOSAGE

Oral doses of nystatin in excess of five million units daily have caused nausea and gastrointestinal upset. There have been no reports of serious toxic effects of superinfections (see CLINICAL PHARMACOLOGY, Pharmacokinetics).

DOSAGE AND ADMINISTRATION

The usual therapeutic dosage is one to two tablets (500,000 to 1,000,000 units nystatin) three times daily. Treatment should generally be continued for at least 48 hours after clinical cure to prevent relapse.

HOW SUPPLIED

Nystatin Tablets, USP 500,000 Units are round brown, film-coated tablets debossed "HP51" on one side and plain on the other side are packaged in:
Bottles of 90: NDC 62135-741-90

Store at 20° to 25°C (68° to 77°F). [See USP Controlled Room Temperature].

Manufactured by:
Vivimed Life Sciences Private Limited
Alathur, Kanchipuram – 603 110, Tamilnadu, India.
M.L. No.: TN00002327

Manufactured for:
Chartwell RX, LLC.
Congers, NY 10920

Revised: 08/2023

L71669

PRINCIPAL DISPLAY PANEL

Nystatin Tablets, USP (Oral), 500,000 units - NDC 62135-741-90 - 90's Bottle Label